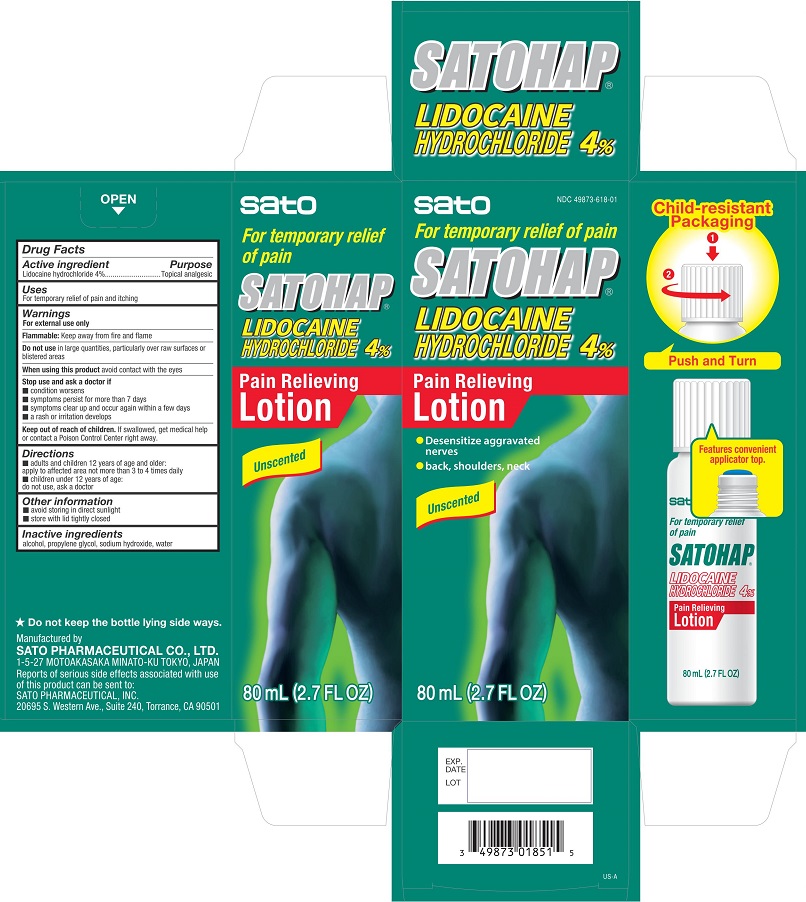 DRUG LABEL: Satohap Lidocaine Hydrochloride 4 Percent Pain Relieving	
NDC: 49873-618 | Form: LOTION
Manufacturer: Sato Pharmaceutical Co., Ltd.
Category: otc | Type: HUMAN OTC DRUG LABEL
Date: 20241231

ACTIVE INGREDIENTS: LIDOCAINE HYDROCHLORIDE 4 g/100 mL
INACTIVE INGREDIENTS: ALCOHOL; PROPYLENE GLYCOL; SODIUM HYDROXIDE; WATER

Satohap Lidocaine HCl 4% Pain Relieving Lotion

Active ingredients

Lidocaine hydrochloride 4%

Purpose

Lidocaine hydrochloride - Topical analgesic

Uses

For temporary relief of pain and itching

Warnings

For external use only

Flammable: Keep away from fire and flame

Do not use in large quantities, particularly over raw surfaces or blistered areas

When using this product avoid contact with the eyes

Stop use and ask a doctor if

- condition worsens
- symptoms persist for more than 7 days
- symptoms clear up and occur again within a few days
- a rash or irritation develops

Keep out of reach of children. If swallowed, get medical help or contact a Poison Control Center right away.

Directions

- adults and children 12 years of age and older: apply to affected area not more than 3 to 4 times dailly
- children under 12 years of age: do not use, ask a doctor

Other information

- avoid storing in direct sunlight
- store with lid tightly closed

INACTIVE INGREDIENT

Inactive ingredients alcohol, propylene glycol, sodium hydroxide, water